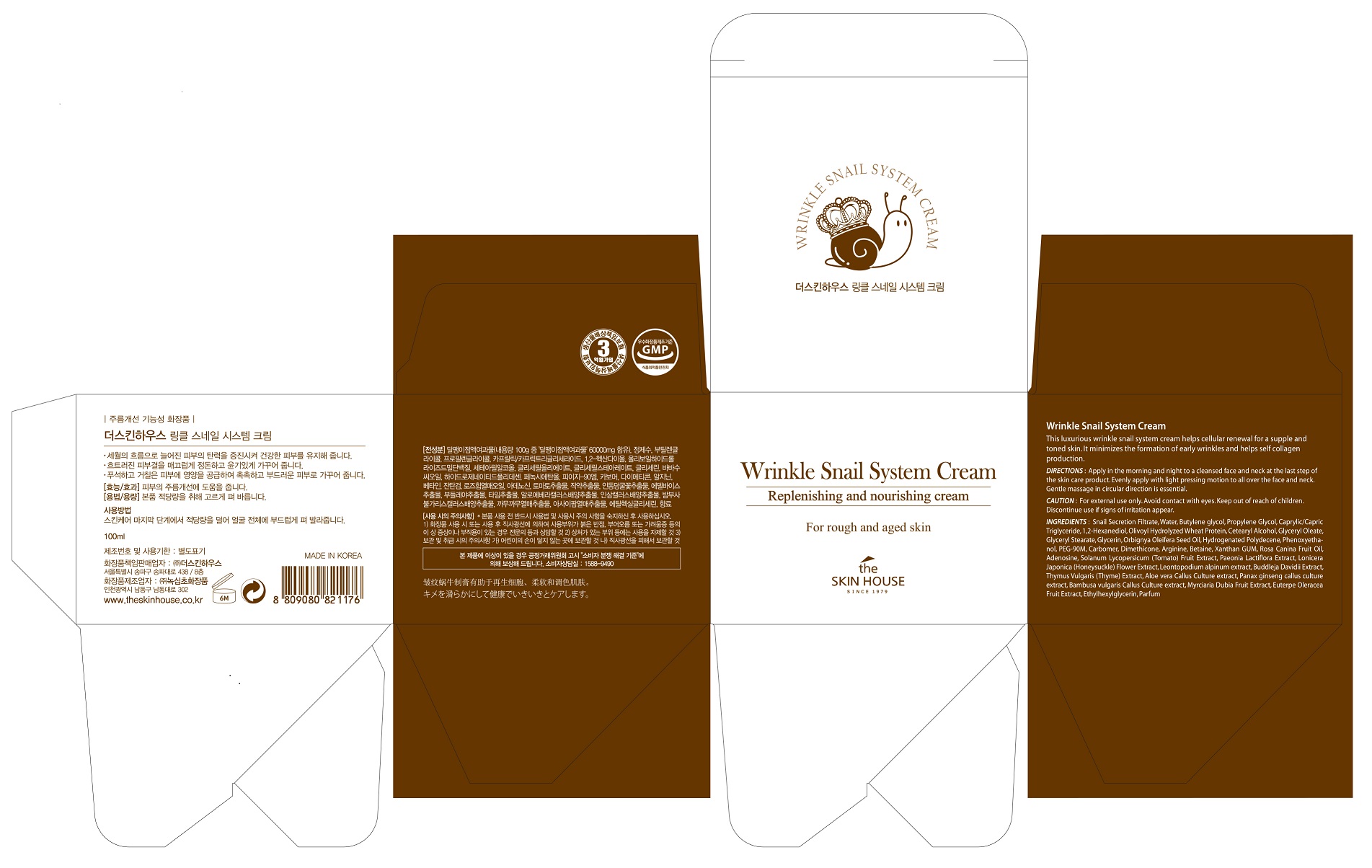 DRUG LABEL: THE SKIN HOUSE Wrinkle Snail SystemCream
NDC: 73590-0032 | Form: CREAM
Manufacturer: NOKSIBCHO cosmetic Co., Ltd.
Category: otc | Type: HUMAN OTC DRUG LABEL
Date: 20200513

ACTIVE INGREDIENTS: ADENOSINE 0.04 g/100 mL
INACTIVE INGREDIENTS: WATER

Drug Facts

ACTIVE INGREDIENT

adenosine

INACTIVE INGREDIENT

Snail Secretion Filtrate
Water
Butylene glycol
Dipropylene Glycol
Caprylic/Capric Triglyceride
1,2-Hexanediol
Olivoyl Hydrolyzed Wheat Protein
Glyceryl Oleate
Glyceryl Stearate
Glycerin
Orbignya Oleifera Seed Oil
Hydrogenated Polydecene
Phenoxyethanol
PEG-90M
Carbomer
Dimethicone
Cetearyl Alcohol
Arginine
Betaine
Xanthan GUM
Rosa Canina Fruit Oil
Solanum Lycopersicum (Tomato) Fruit Extract
Paeonia Lactiflora Extract
Lonicera Japonica (Honeysuckle) Flower Extract
Leontopodium alpinum extract
Buddleja Davidii Extract
Buddleja Davidii Extract
Thymus Vulgaris (Thyme) Extract
Aloe Barbadensis Callus Culture Extract
Panax ginseng callus culture extract
Bambusa vulgaris Callus Culture extract
Myrciaria Dubia Fruit Extract
Euterpe Oleracea Fruit Extract
Ethylhexylglycerin
Parfum

PURPOSE

wrinkle care

keep out of reach of the children

INDICATIONS AND USAGE

apply proper amount to the skin

WARNINGS

For external use only
When using this product

■ if the following symptoms occurs after use, stop use and consult with a skin specialist

red specks, swelling, itching

■ don’t use on the part where there is injury, eczema, or dermatitis

Keep out of reach of children

■ if swallowed, get medical help or contact a person control center immediately